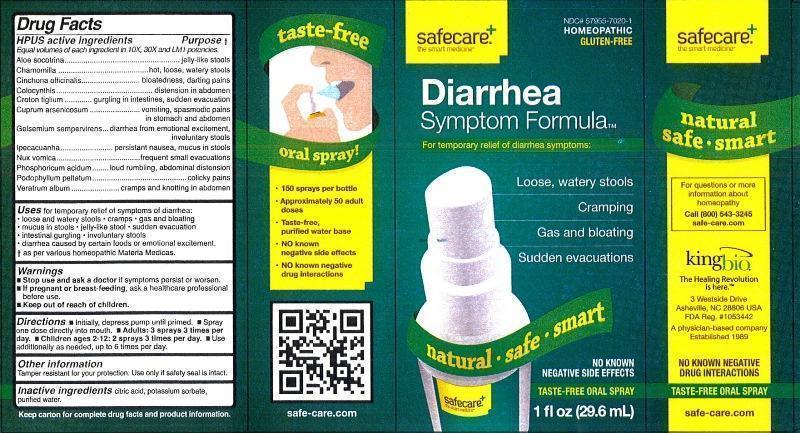 DRUG LABEL: Diarrhea Symptom Formula
NDC: 57955-7020 | Form: LIQUID
Manufacturer: King Bio Inc.
Category: homeopathic | Type: HUMAN OTC DRUG LABEL
Date: 20130220

ACTIVE INGREDIENTS: ALOE 10 [hp_X]/29.6 mL; MATRICARIA RECUTITA 10 [hp_X]/29.6 mL; CINCHONA OFFICINALIS BARK 10 [hp_X]/29.6 mL; CITRULLUS COLOCYNTHIS FRUIT PULP 10 [hp_X]/29.6 mL; CROTON TIGLIUM SEED 10 [hp_X]/29.6 mL; CUPRIC ARSENITE 10 [hp_X]/29.6 mL; GELSEMIUM SEMPERVIRENS ROOT 10 [hp_X]/29.6 mL; IPECAC 10 [hp_X]/29.6 mL; STRYCHNOS NUX-VOMICA SEED 10 [hp_X]/29.6 mL; PHOSPHORIC ACID 10 [hp_X]/29.6 mL; PODOPHYLLUM 10 [hp_X]/29.6 mL; VERATRUM ALBUM ROOT 10 [hp_X]/29.6 mL
INACTIVE INGREDIENTS: CITRIC ACID MONOHYDRATE; POTASSIUM SORBATE; WATER

Diarrhea Symptom Formula

Active Ingredients

HPUS active ingredients

Equal volumes of each ingredient in 10X, 30X and LM1 potencies.

Aloe socotrina, Chamomilla, Cinchona officinalis, Colocynthis, Croton tiglium, Cuprum arsenicosum, Gelsemium sempervirens, Ipecacuanha, Nux vomica, Phosphoricum acidum, Podophyllum peltatum, veratrum album

Inactive Ingredients citric acid, potassium sorbate, purified water

Purpose

HPUS active ingredients Purpose†

Equal volumes of each ingredient in 10X, 30X and LM1 potencies.

Aloe socotrina................................................................jelly-like stools

Chamomilla....................................................................hot, loose, watery stools

Cinchona officinalis........................................................bloatedness, darting pains

Colocynthis....................................................................distension in abdomen

Croton tiglium................................................................gurgling in intestines, sudden evacuation

Cuprum arsenicosum.....................................................vomiting, spasmodic pains in stomach and abdomen

Gelsemium sempervirens...............................................diarrhea from emotional excitement, involumtary stools

Ipecacuanha..................................................................persistant nausea, mucus in stools

Nux vomica.....................................................................frequent small evacuations

Phosphoricum acidum.....................................................loud rumbling, abdominal distension

Podophyllum peltatum....................................................colicky pains

Veratrum album..............................................................cramps and knotting in abdomen

Indications and Usage

Uses for temporary relief of symptoms of diarrhea:

- loose and watery stools
- cramps
- gas and bloating
- mucus in stools
- jelly-like stool
- sudden evacuation
- intestinal gurgling
- involuntary stools
- diarrhea caused by certain foods or emotional excitement.

† as per various homeopathic Materia Medicas.

Warnings

- Stop use and ask a doctor if symptoms persist or worsen.
- If pregnant or breast-feeding, ask a healthcare professional before use.
- Keep out of reach of children.

Other information

Tamper resistant for your protection. Use only if safety seal is intact.

Keep out of reach of children.

Dosage and Administration

Directions

- Initially, depress pump until primed.
- Spray one dose directly into mouth.
- Adults: 3 sprays 3 times per day.
- Children ages 2-12: 2 sprays 3 times per day.
- Use additionally as needed, up to 6 times per day.

PACKAGE LABEL

3 Westside Drive

Asheville, NC 28806

For questions or more information about homeopathy call (800) 543-3245 or safe-care.com